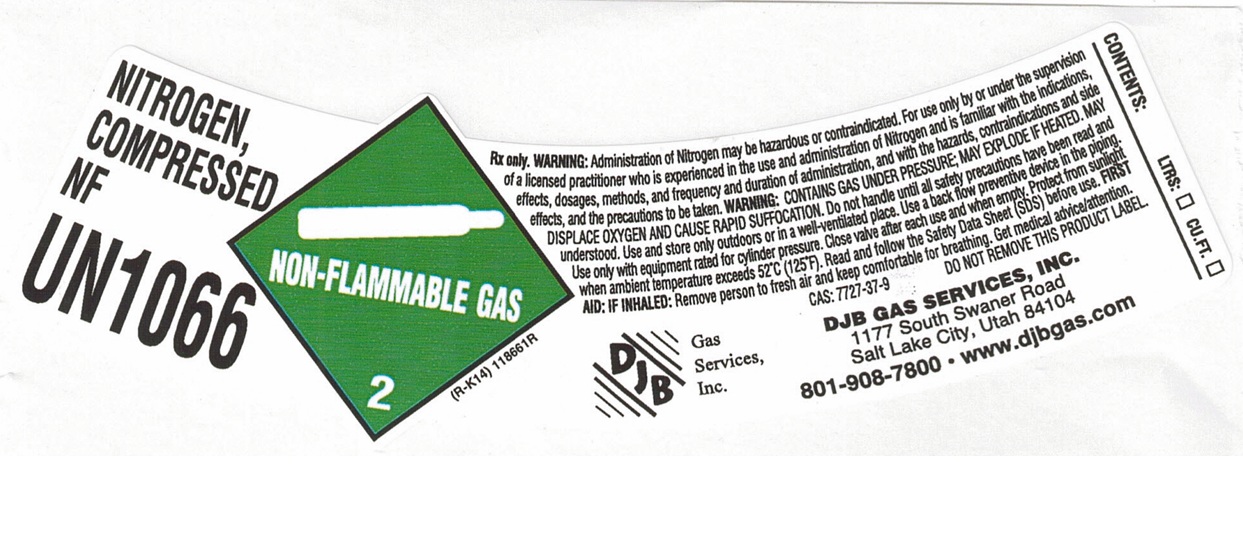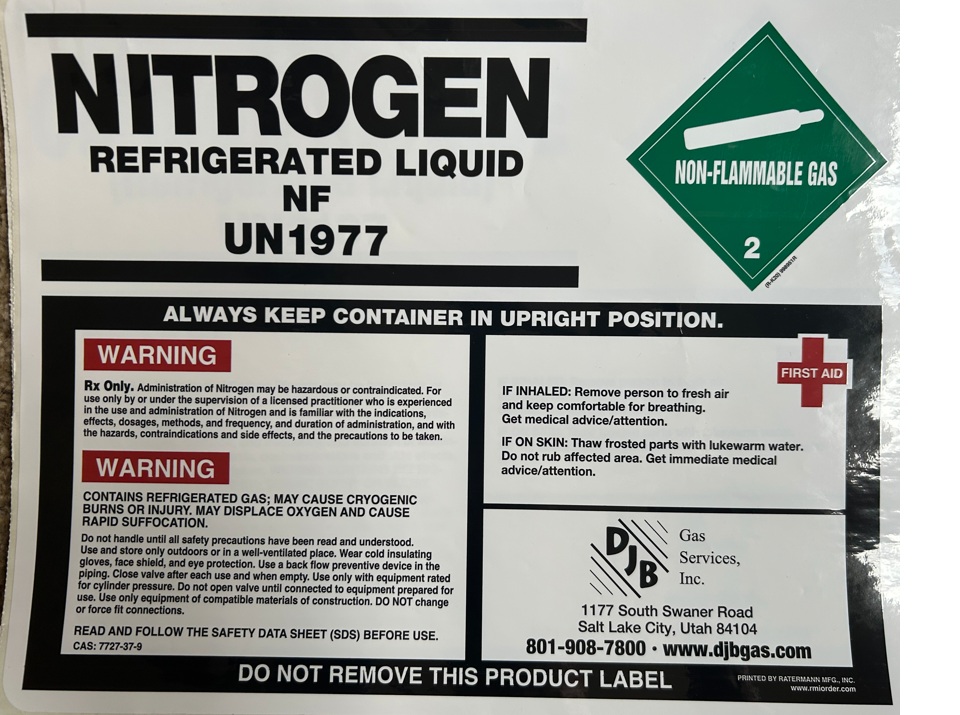 DRUG LABEL: Nitrogen
NDC: 43621-002 | Form: GAS
Manufacturer: DJB Gas Services, Inc
Category: prescription | Type: HUMAN PRESCRIPTION DRUG LABEL
Date: 20260226

ACTIVE INGREDIENTS: NITROGEN 990 mL/1 L

Nitrogen

PACKAGE LABEL

NITROGEN, COMPRESSED NF

UN1066

Rx only. WARNING: Administration of Nitrogen may be hazardous or contraindicated. For use only by or under the supervision of a licensed practitioner who is experienced in the use and administration of Nitrogen and is familiar with the indications, effects, dosages, methods, and frequency and duration of administration, and with the hazards, contraindications and side effects, and the precautions to be taken. WARNING: CONTAINS GAS UNDER PRESSURE; MAY EXPLODE IF HEATED. MAY DISPLACE OXYGEN AND CAUSE RAPID SUFFOCATION. Do not handle until all safety precautions have been read and understood. Use and store only outdoors or in a well-ventilated place. Use a back flow preventive device in the piping. Use only with equipment rated for cylinder pressure. Close valve after each use and when empty. Protect from sunlight when ambient temperature exceeds 52 C (125 F). Read and follow the Safety Data Sheet (SDS) before use. FIRST AID: IF INHALED: Remove person to fresh air and keep comfortable for breathing. Get medical advice/attention.

CAS: 7727-37-9 DO NOT REMOVE THIS PRODUCT LABEL.

DJB Gas Services, Inc.

DJB GAS SERVICES, INC.

1177 Swaner Road

Salt Lake City, UT 84104

801-908-7800 www.djbgas.com

CONTENTS: LTRS: CU.FT.

PACKAGE LABEL

NITROGEN REFRIGERATED LIQUID NF

UN1977

ALWAYS KEEP CONTAINER IN UPRIGHT POSITION.

WARNING

Rx Only. Administration of Nitrogen may be hazardous or contraindicated. For use only by or under the supervision of a licensed practitioner who is experienced in the use and administration of Nitrogen and is familiar with the indications, effects, dosages, methods, and frequency, and duration of administration, and with the hazards, contraindications and side effects, and the precautions to be taken.

WARNING

CONTAINS REFRIGERATED GAS; MAY CAUSE CRYOGENIC BURNS OR INJURY. MAY DISPLACE OXYGEN AND CAUSE RAPID SUFFOCATION.

Do not handle until all safety precautions have been read and understood. Use and store only outdoors or in a well-ventilated place. Wear cold insulating gloves, face shield, and eye protection. Use a back flow preventive device in the piping. Close valve after each use and when empty. Use only with equipment rated for cylinder pressure. Do not open valve until connected to equipment prepared for use. Use only equipment of compatible materials of construction. DO NOT change or force fit connections.

READ AND FOLLOW THE SAFETY DATA SHEET (SDS) BEFORE USE.

CAS: 7727-37-9

FIRST AID

IF INHALED: Remove person to fresh air and keep comfortable for breathing. Get medical advice/attention.

IF ON SKIN: Thaw frosted parts with lukewarm water. Do not rub affected area. Get immediate medical advice/attention.

DJB Gas Services, Inc.

1177 Swaner Road

Salt Lake City, UT 84104

801-908-7800 www.djbgas.com

DO NOT REMOVE THIS PRODUCT LABEL